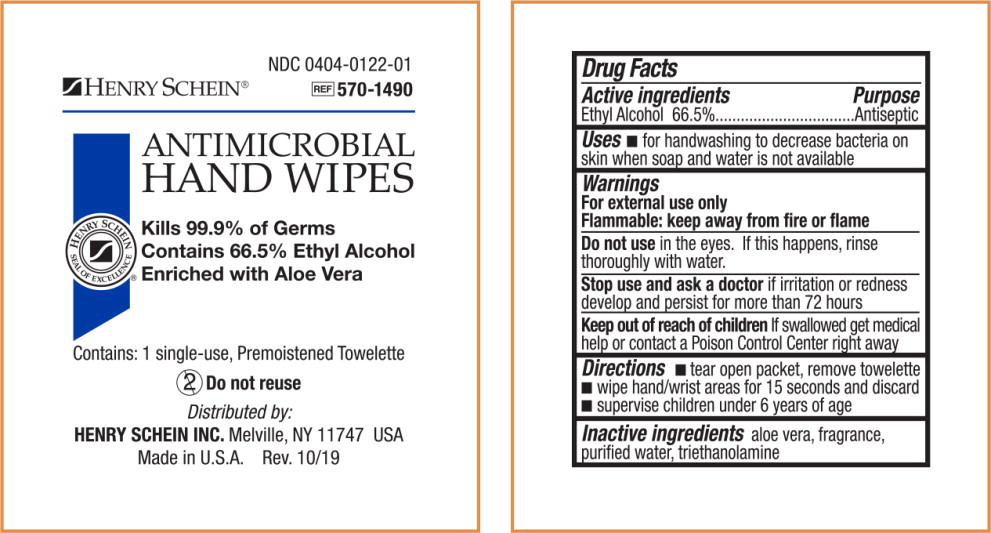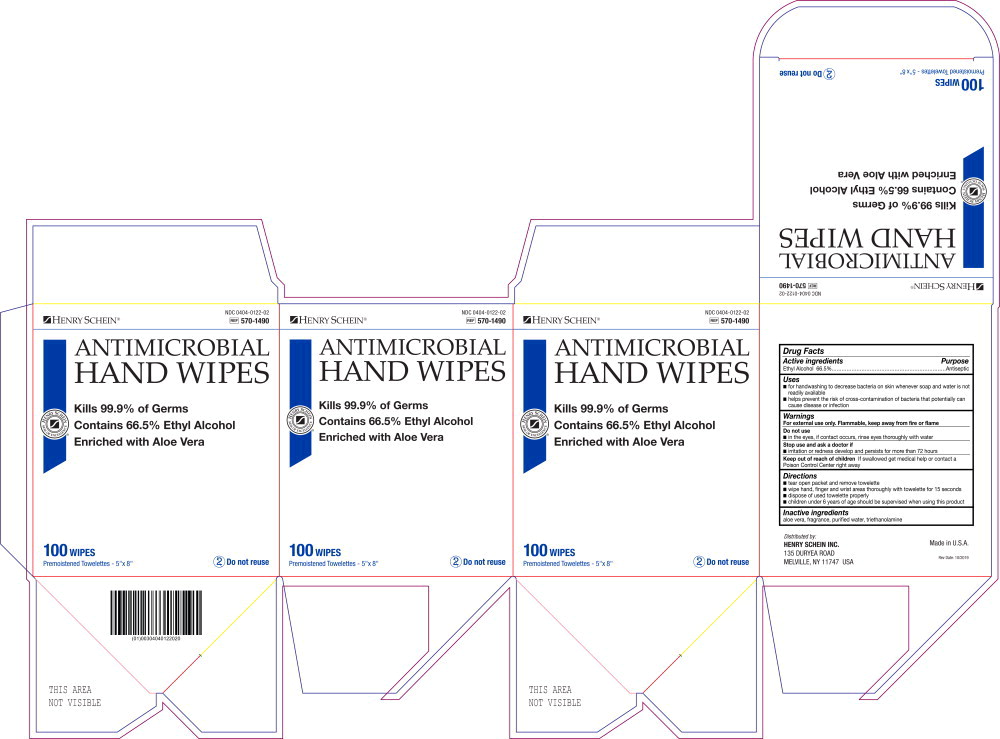 DRUG LABEL: Antibacterial
NDC: 0404-0122 | Form: LIQUID
Manufacturer: Henry Schein Inc.
Category: otc | Type: HUMAN OTC DRUG LABEL
Date: 20250110

ACTIVE INGREDIENTS: ALCOHOL 665 mL/1 L
INACTIVE INGREDIENTS: ALOE; WATER; TROLAMINE

0404-0122 Antimicrobial Hand Wipe

Drug Facts

Active ingredients

Ethyl Alcohol 66.5%

Purpose

Antiseptic

Uses

- for handwashing to decrease bacteria on skin whenever soap and water is not readily available
- helps prevent the risk of cross-contamination of bacteria that potentially can cause disease or infection

Warnings

For external use only. Flammable, keep away from fire or flame

Do not use

- in the eyes, if contact occurs, rinse eyes thoroughly with water

Stop use and ask a doctor if

- irritation or redness develop and persists for more than 72 hours

Keep out of reach of children

If swallowed get medical help or contact a Poison Control Center right away

Directions

- tear open packet and remove towelette
- wipe hand, finger and wrist areas thoroughly with towelette for 15 seconds
- dispose of used towelette properly
- children under 6 years of age should be supervised when using this product

Inactive ingredients

aloe vera, fragrance, purified water, triethanolamine

Principal Display Panel - Pouch Label

HENRY SCHEIN®

NDC 0404-0122-01

REF 570-1490

ANTIMICROBIAL
HAND WIPES

HERNY SCHEIN

SEAL OF EXCELLENCE®

Kills 99.9% of Germs

Contains 66.5% Ethyl Alcohol

Enriched with Aloe Vera

Contains: 1 single-use, Premoistened Towelette

2 Do not reuse

Distributed by:

HENRY SCHEIN INC.Melville, NY 11747 USA

Made in U.S.A. Rev. 10/19

Principal Display Panel - Box Label

HENRY SCHEIN®

NDC 0404-0122-02

REF 570-1490

ANTIMICROBIAL
HAND WIPES

HERNY SCHEIN

SEAL OF EXCELLENCE®

Kills 99.9% of Germs

Contains 66.5% Ethyl Alcohol

Enriched with Aloe Vera

100 WIPES

Premoistened Toweletts - 5" x 8"

2 Do not reuse